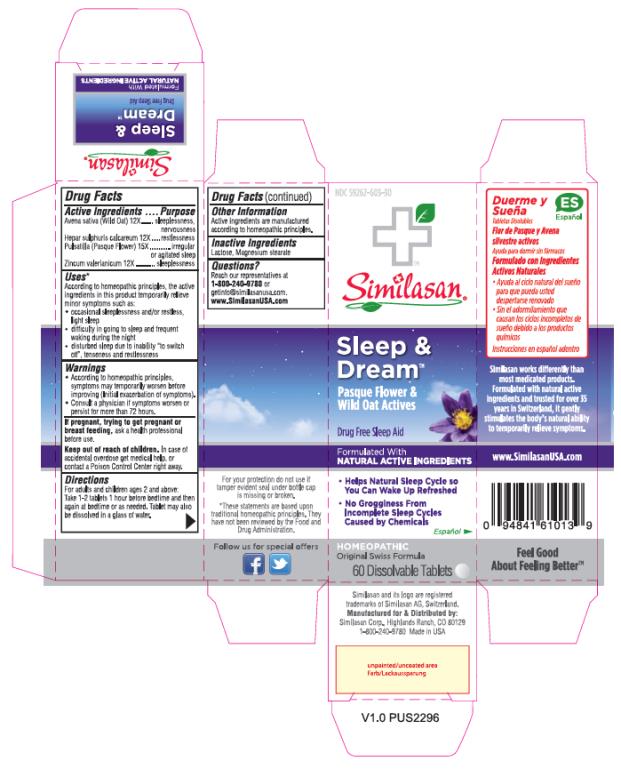 DRUG LABEL: Sleep and Dream
NDC: 59262-303 | Form: TABLET
Manufacturer: Similasan Corporation
Category: homeopathic | Type: HUMAN OTC DRUG LABEL
Date: 20161212

ACTIVE INGREDIENTS: AVENA SATIVA FLOWERING TOP 12 [hp_X]/1 1; CALCIUM SULFIDE 12 [hp_X]/1 1; ANEMONE PULSATILLA 15 [hp_X]/1 1; ZINC VALERATE DIHYDRATE 12 [hp_X]/1 1
INACTIVE INGREDIENTS: LACTOSE; MAGNESIUM STEARATE

Sleep and Dream

Sleep & Dream

Drug Facts

Active Ingredients

Avena sativa (Wild Oat) 12X

Purpose

sleeplessness, nervousness

Active Ingredients

Hepar sulphuris calcareum 12X

Purpose

restlessness

Active Ingredients

Pulsatilla (Pasque Flower) 15X

Purpose

irregular or agitated sleep

Active Ingredients

Zincum valerianicum 12X

Purpose

sleeplessness

Uses*

According to homeopathic principles, the active ingredients in this product temporarily relieve minor symptoms such as:

• occasional sleeplessness and/or restless, light sleep

• difficulty in going to sleep and frequent waking during the night

• disturbed sleep due to inability “to switch off”, tenseness and restlessness

Warnings

• According to homeopathic principles, symptoms may temporarily worsen before improving (Initial exacerbation of symptoms).

• Consult a physician if symptoms worsen or persist for more than 72 hours.

Keep out of reach of children.

In case of accidental overdose get medical help, or contact a Poison Control Center right away.

Directions

For adults and children ages 2 and above:

Take 1-2 tablets 1 hour before bedtime and then again at bedtime or as needed. Tablet may also be dissolved in a glass of water.

Other Information

Active ingredients are manufactured according to homeopathic principles.

Inactive Ingredients

Lactose, Magnesium stearate

Questions?

Reach our representatives at 1-800-240-9780 or getinfo@similasanusa.com.

www.SimilasanUSA.com

*These statements are based upon traditional homeopathic principles. They have not been reviewed by the Food and Drug Administration.

PRINCIPAL DISPLAY PANEL

NDC 59262-603-30
Sleep & Dream
Pasque Flower &
Wild Oat Actives
60 Dissolvable Tablets